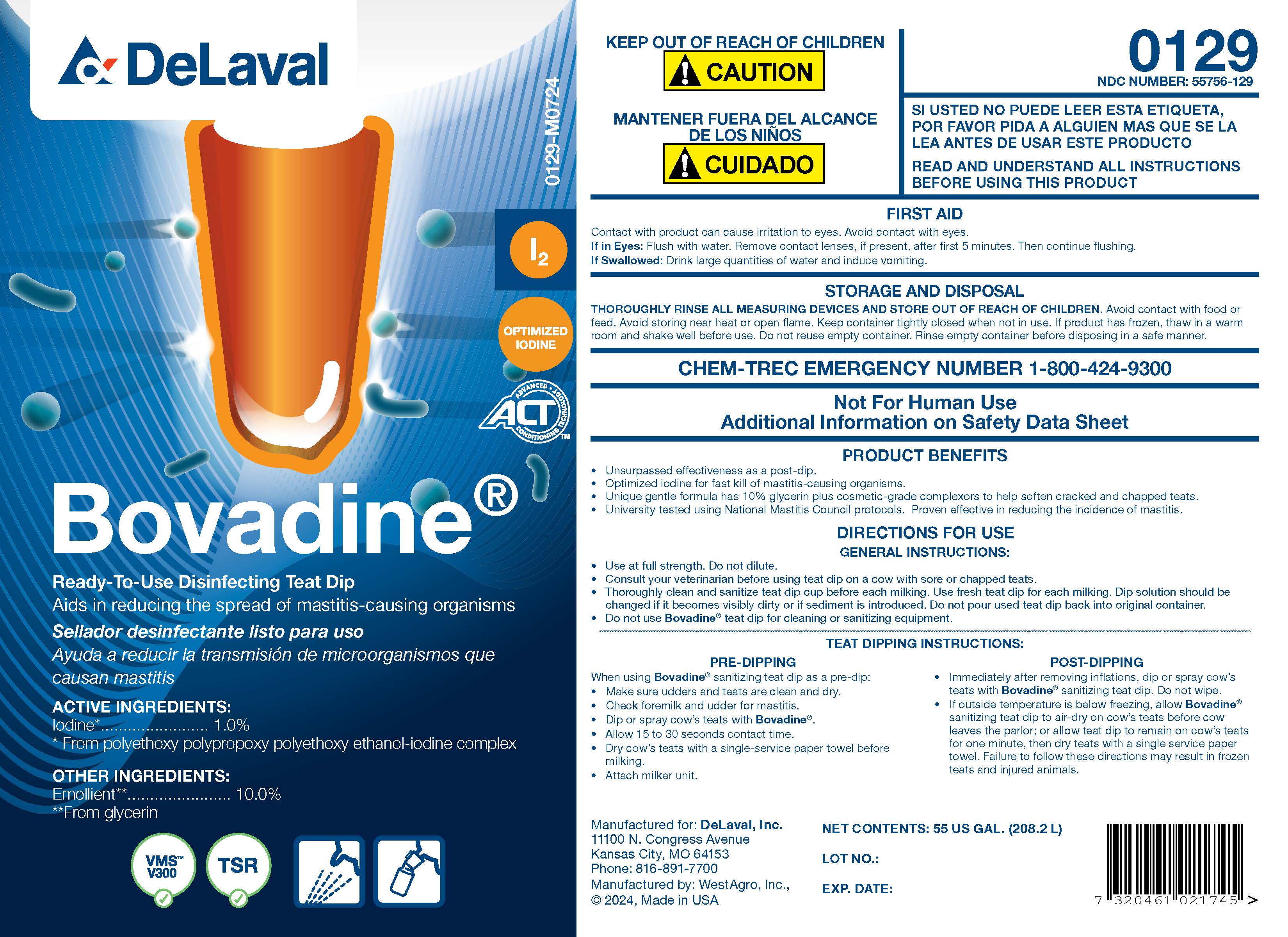 DRUG LABEL: Bovadine
NDC: 55756-129 | Form: SOLUTION
Manufacturer: DeLaval, Inc.
Category: animal | Type: OTC ANIMAL DRUG LABEL
Date: 20251017

ACTIVE INGREDIENTS: IODINE 10.5 g/1 L
INACTIVE INGREDIENTS: DOCUSATE SODIUM; SODIUM HYDROXIDE; ANHYDROUS CITRIC ACID; GLYCERIN; XANTHAN GUM; POLOXAMER 403; SODIUM IODATE; SODIUM IODIDE; WATER; POLOXAMER 335; SODIUM CHLORIDE

Bovadine

PURPOSE

Ready-To-Use Disinfecting Teat Dip

Aids in reducing the spread of mastitis-causing orgamisms

ACTIVE INGREDIENTS:
Iodine*......................................................... 1.0%
* From polyethoxy polypropoxy polyethoxy ethanol-iodine Complex

INACTIVE INGREDIENT

OTHER INGREDIENTS:

Emollient**......................... 10.0%

**From glycerin

PRODUCT BENEFITS

- Unsurpassed effectiveness as a post-dip.
- Optimized iodine for fast kill of mastitis-causing organisms.
- Unique gentle formula has 10% glycerin plus cosmetic-grade complexors to help soften cracked and chapped teats.
- University tested using National Mastitis Council protocols. Proven effective in reducing the incidence of mastitis.

INDICATIONS AND USAGE

DIRECTIONS FOR USE
GENERAL INSTRUCTIONS

- Use at full strength. Do not dilute.
- Consult your veterinarian before using teat dip on a cow with sore or chapped teats.
- Thoroughly clean and sanitize teat dip cup before each milking. Use fresh teat dip for each milking. Dip solution should be changed if it becomes visibly dirty, or if sediment is introduced. Do not pour used teat dip back into original container.
- Do not use Bovadine® teat dip for cleaning or sanitizing equipment.

TEAT DIPPING INSTRUCTIONS:
PRE-DIPPING

When using Bovidine® sanitizing teat dip as a pre-dip:

- Make sure udder and teats are clean and dry.
- Check foremilk and udder for mastitis.
- Dip or spray cow's teats with Bovadine®.
- Allow 15 to 30 seconds contact time.
- Dry cow's teats with a single-service paper towel before milking.
- Attach milker unit.

POST-DIPPING

- Immediately after removing inflations, dip or spray cow's teats with Bovadine® santizing teat dip. Do not wipe.
- If outside temperature is below freezing, allow Bovadine® santizing teat dip to air-dry on cow's teats before cow leaves the parlor; or allow teat dip to remain on cow's teats for one minute, then dry teats with a single service paper towel. Failure to follow these directions may result in frozen teats and injured animals.

KEEP OUT OF REACH OF CHILDREN

! CAUTION

MANTENER FUERA DEL ALCANCE DE LOS NINOS

! CUIDADO

READ AND UNDERSTAND ALL INSTRUCTIONS BEFORE USING THIS PRODUCT

FIRST AID

Contact with product can cause irritation to eyes. Avoid contact with eyes.
In in Eyes: Flush with water. Remove contact lenses, if present, after first 5 minutes. Then continue flushing.
If Swallowed: Drink large quantities of water and induce vomiting.

NOT FOR HUMAN USE

ADDITIONAL INFORMATION ON SAFETY DATA SHEET

STORAGE AND DISPOSAL

THOROUGHLY RINSE ALL MEASURING DEVICES AND STORE OUT OF REACH OF CHILDREN. Avoid contact with food or feed. Avoid storing near heat or open flame. Keep container tightly closed when not in use. If product has frozen, thaw in a warm room and shake well before use. Do not reuse empty container. Rinse empty container before disposing in a safe manner.

CHEMTREC EMERGENCY NUMBER 1-800-424-9300

NET CONTENTS:

LOT NO.:

EXP. DATE: